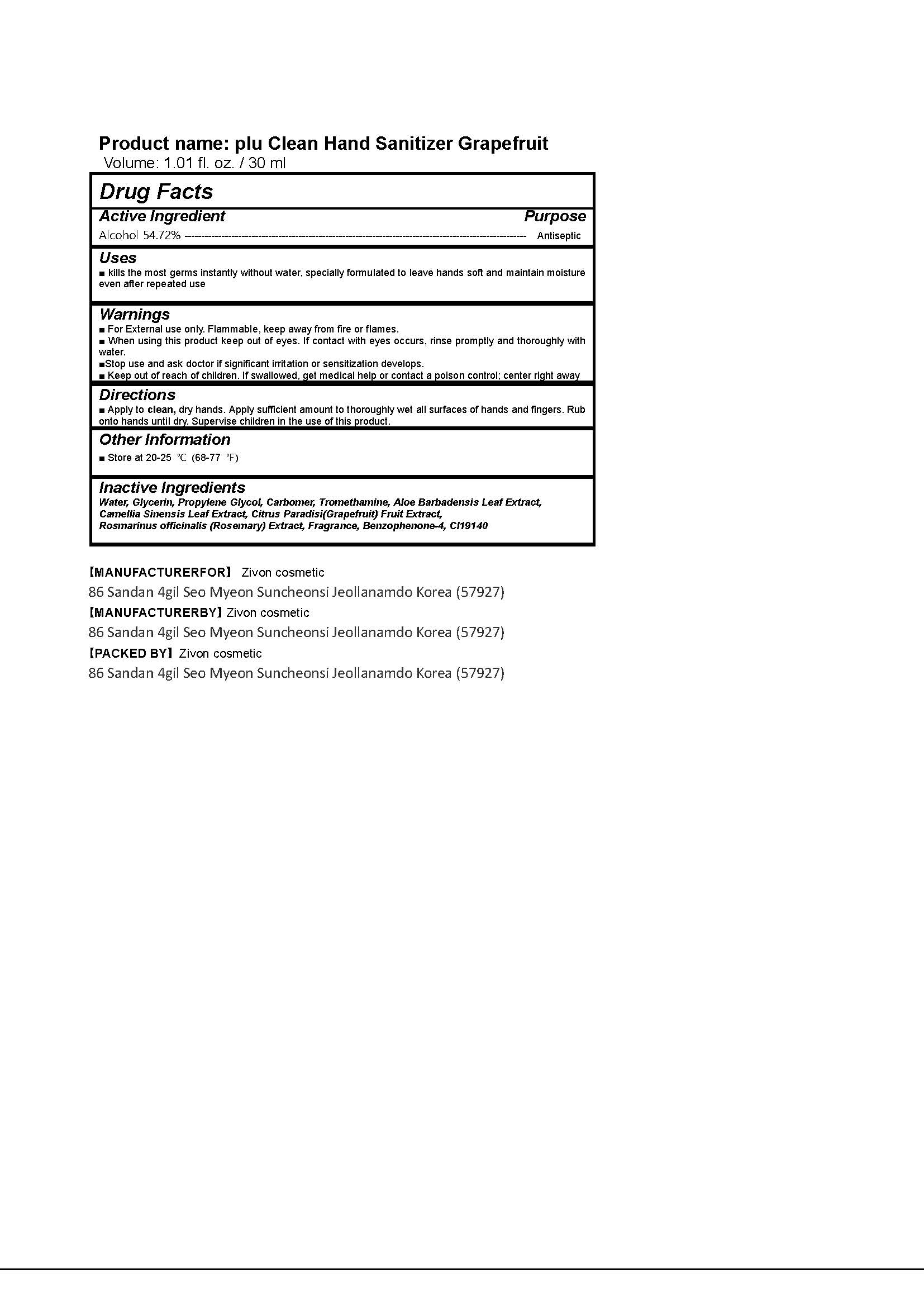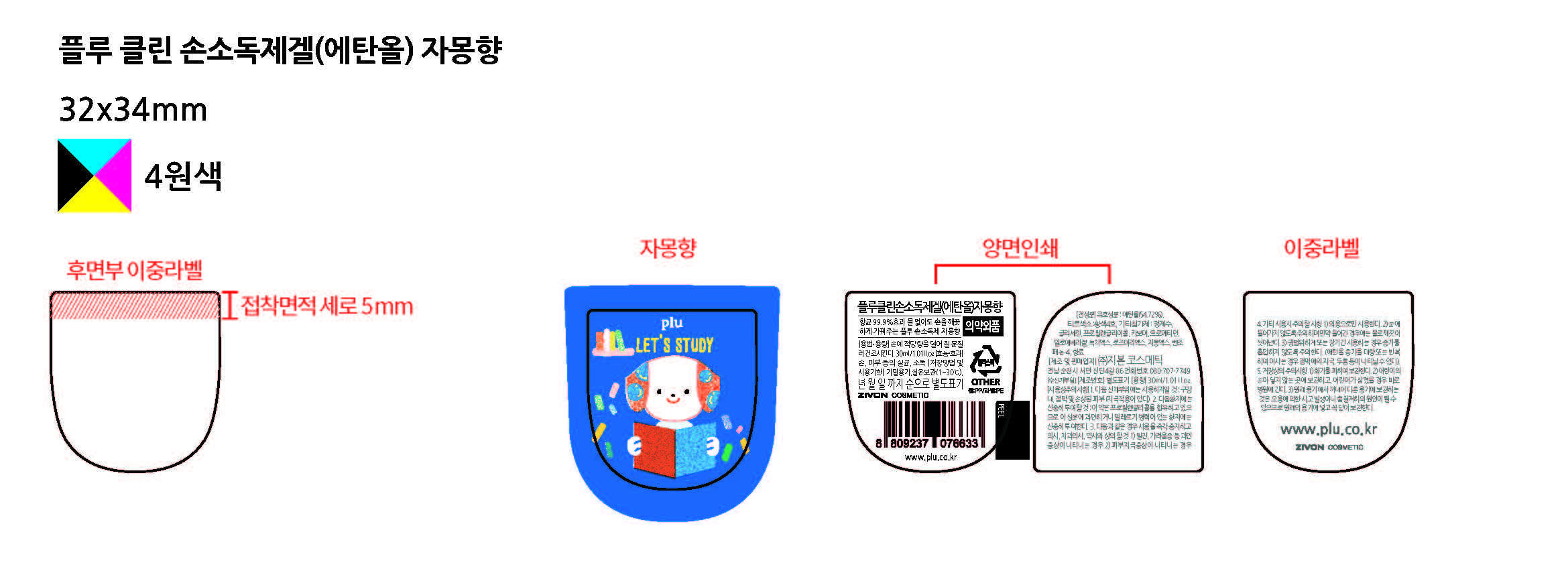 DRUG LABEL: Plu Clean Hand Sanitizer Gel Grapefruit
NDC: 71503-110 | Form: GEL
Manufacturer: Zivon Cosmetic Co., Ltd.
Category: otc | Type: HUMAN OTC DRUG LABEL
Date: 20200507

ACTIVE INGREDIENTS: ALCOHOL 16.2 mL/30 mL
INACTIVE INGREDIENTS: ALOE; WATER; GLYCERIN

Drug Facts

ACTIVE INGREDIENT

Alcohol

INACTIVE INGREDIENT

Water, Glycerin, Propylene Glycol, Carbomer, Tromethamine, Aloe Barbadensis Leaf Extract,

Camellia Sinensis Leaf Extract, Citrus Paradisi(Grapefruit) Fruit Extract,

Rosmarinus officinalis (Rosemary) Extract, Fragrance, Benzophenone-4, CI19140

PURPOSE

Antiseptic

KEEP OUT OF REACH OF THE CHILDREN

INDICATIONS AND USAGE

For the external use only

WARNINGS

■ For External use only. Flammable, keep away from fire or flames.

■ When using this product keep out of eyes. If contact with eyes occurs, rinse promptly and thoroughly with water.

■Stop use and ask doctor if significant irritation or sensitization develops.

■ Keep out of reach of children. If swallowed, get medical help or contact a poison control; center right away

DOSAGE AND ADMINISTRATION

■ Apply to clean, dry hands. Apply sufficient amount to thoroughly wet all surfaces of hands and fingers. Rub onto hands until dry. Supervise children in the use of this product.